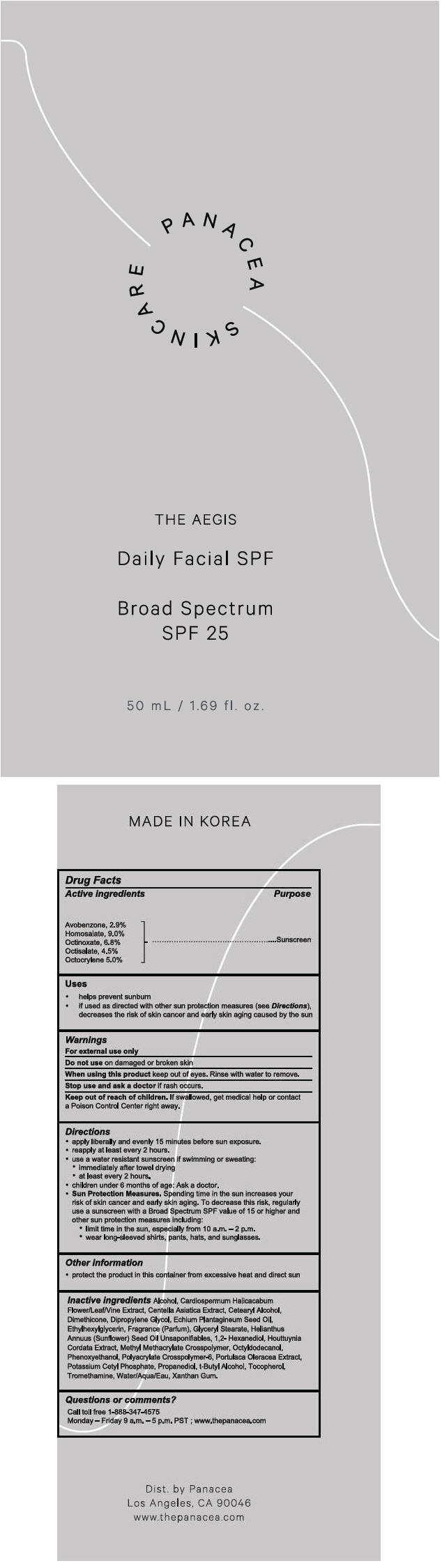 DRUG LABEL: Aegis Daily Facial 
NDC: 71690-201 | Form: LOTION
Manufacturer: JNTLee Inc. dba Panacea
Category: otc | Type: HUMAN OTC DRUG LABEL
Date: 20170831

ACTIVE INGREDIENTS: AVOBENZONE 29 mg/1 mL; HOMOSALATE 90 mg/1 mL; OCTINOXATE 68 mg/1 mL; OCTISALATE 45 mg/1 mL; OCTOCRYLENE 50 mg/1 mL
INACTIVE INGREDIENTS: ALCOHOL; CARDIOSPERMUM HALICACABUM FLOWERING TOP; CENTELLA ASIATICA; CETOSTEARYL ALCOHOL; DIMETHICONE; DIPROPYLENE GLYCOL; ECHIUM PLANTAGINEUM SEED OIL; ETHYLHEXYLGLYCERIN; GLYCERYL MONOSTEARATE; SUNFLOWER OIL; 1,2-HEXANEDIOL; HOUTTUYNIA CORDATA FLOWERING TOP; METHYL METHACRYLATE/GLYCOL DIMETHACRYLATE CROSSPOLYMER; OCTYLDODECANOL; PHENOXYETHANOL; PURSLANE; POTASSIUM CETYL PHOSPHATE; PROPANEDIOL; TERT-BUTYL ALCOHOL; TOCOPHEROL; TROMETHAMINE; WATER; XANTHAN GUM

Aegis Daily Facial SPF
SPF 25

Drug Facts

Active ingredients

Avobenzone, 2.9%
Homosalate, 9.0%
Octinoxate, 6.8%
Octisalate, 4.5%
Octocrylene 5.0%

Purpose

Sunscreen

Uses

- helps prevent sunburn
- if used as directed with other sun protection measures (see Directions), decreases the risk of skin cancer and early skin aging caused by the sun

Warnings

For external use only

Do not use on damaged or broken skin

When using this product keep out of eyes. Rinse with water to remove.

Stop use and ask a doctor if rash occurs.

Keep out of reach of children. If swallowed, get medical help or contact a Poison Control Center right away.

Directions

- apply liberally and evenly 15 minutes before sun exposure.
- reapply at least every 2 hours.
- use a water resistant sunscreen if swimming or sweating:
  - immediately after towel drying
  - at least every 2 hours.
- children under 6 months of age: Ask a doctor.
- Sun Protection Measures. Spending time in the sun increases your risk of skin cancer and early skin aging. To decrease this risk, regularly use a sunscreen with a Broad Spectrum SPF value of 15 or higher and other sun protection measures including:
  - limit time in the sun, especially from 10 a.m. – 2 p.m.
  - wear long-sleeved shirts, pants, hats, and sunglasses.

Other information

- protect the product in this container from excessive heat and direct sun

Inactive ingredients

Alcohol, Cardiospermum Halicacabum Flower/Leaf/Vine Extract, Centella Asiatica Extract, Cetearyl Alcohol, Dimethicone, Dipropylene Glycol, Echium Plantagineum Seed Oil, Ethylhexylglycerin, Fragrance (Parfum), Glyceryl Stearate, Helianthus Annuus (Sunflower) Seed Oil Unsaponifiables, 1,2- Hexanediol, Houttuynia Cordata Extract, Methyl Methacrylate Crosspolymer, Octyldodecanol, Phenoxyethanol, Polyacrylate Crosspolymer-6, Portulaca Oleracea Extract, Potassium Cetyl Phosphate, Propanediol, t-Butyl Alcohol, Tocopherol, Tromethamine, Water/Aqua/Eau, Xanthan Gum.

Questions or comments?

Call toll free 1-888-347-4575

Monday – Friday 9 a.m. – 5 p.m. PST ; www.thepanacea.com

Dist. by Panacea
Los Angeles, CA 90046

PRINCIPAL DISPLAY PANEL - 50 mL Bottle Label

PANACEA
SKINCARE

THE AEGIS

Daily Facial SPF

Broad Spectrum
SPF 25

50 mL / 1.69 fl. oz.